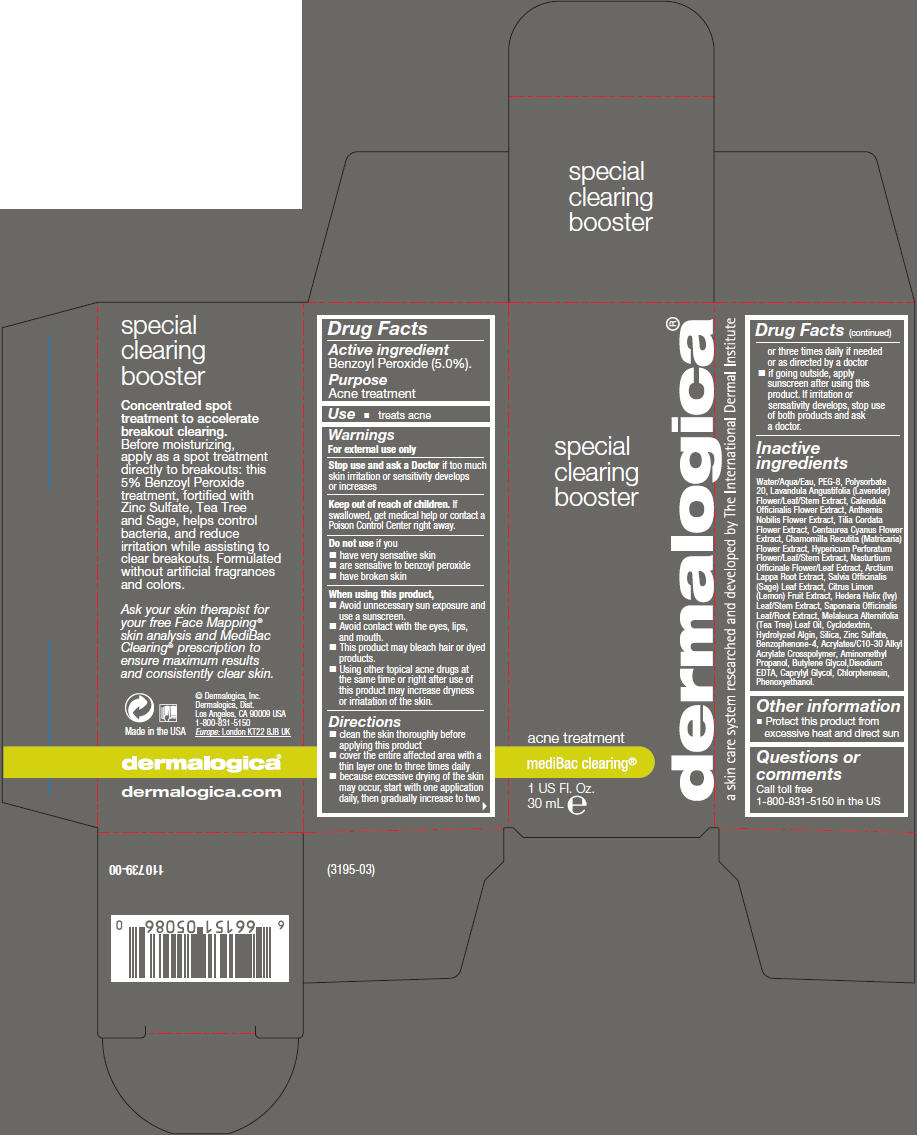 DRUG LABEL: Special Clearing Booster
NDC: 68479-503 | Form: LIQUID
Manufacturer: Dermalogica, Inc.
Category: otc | Type: HUMAN OTC DRUG LABEL
Date: 20151123

ACTIVE INGREDIENTS: Benzoyl Peroxide 50 mg/1 mL
INACTIVE INGREDIENTS: Water; Polyethylene Glycol 400; Polysorbate 20; Lavandula Angustifolia Flowering Top; Calendula Officinalis Flower; Chamaemelum Nobile Flower; Tilia Cordata Flower; Centaurea Cyanus Flower; Chamomile; St. John's Wort; Nasturtium Officinale Flowering Top; Arctium Lappa Root; Sage; Lemon; Hedera Helix Leaf; Saponaria Officinalis Leaf; Tea Tree Oil; Silicon Dioxide; Zinc Sulfate; Sulisobenzone; Carbomer Interpolymer Type A (Allyl Sucrose Crosslinked); Aminomethylpropanol; Butylene Glycol; Edetate Disodium; Caprylyl Glycol; Chlorphenesin; Phenoxyethanol

Special Clearing Booster

Drug Facts

Active ingredient

Benzoyl Peroxide (5.0%).

Purpose

Acne treatment

Use

- treats acne

Warnings

For external use only

Stop use and ask a Doctor if too much skin irritation or sensitivity develops or increases

Keep out of reach of children. If swallowed, get medical help or contact a Poison Control Center right away.

Do not use if you

- have very sensative skin
- are sensative to benzoyl peroxide
- have broken skin

When using this product,

- Avoid unnecessary sun exposure and use a sunscreen.
- Avoid contact with the eyes, lips, and mouth.
- This product may bleach hair or dyed products.
- Using other topical acne drugs at the same time or right after use of this product may increase dryness or irriatation of the skin.

Directions

- clean the skin thoroughly before applying this product
- cover the entire affected area with a thin layer one to three times daily
- because excessive drying of the skin may occur, start with one application daily, then gradually increase to two or three times daily if needed or as directed by a doctor
- if going outside, apply sunscreen after using this product. If irritation or sensativity develops, stop use of both products and ask a doctor.

Inactive ingredients

Water/Aqua/Eau, PEG-8, Polysorbate 20, Lavandula Angustifolia (Lavender) Flower/Leaf/Stem Extract, Calendula Officinalis Flower Extract, Anthemis Nobilis Flower Extract, Tilia Cordata Flower Extract, Centaurea Cyanus Flower Extract, Chamomilla Recutita (Matricaria) Flower Extract, Hypericum Perforatum Flower/Leaf/Stem Extract, Nasturtium Officinale Flower/Leaf Extract, Arctium Lappa Root Extract, Salvia Officinalis (Sage) Leaf Extract, Citrus Limon (Lemon) Fruit Extract, Hedera Helix (Ivy) Leaf/Stem Extract, Saponaria Officinalis Leaf/Root Extract, Melaleuca Alternifolia (Tea Tree) Leaf Oil, Cyclodextrin, Hydrolyzed Algin, Silica, Zinc Sulfate, Benzophenone-4, Acrylates/C10-30 Alkyl Acrylate Crosspolymer, Aminomethyl Propanol, Butylene Glycol,Disodium EDTA, Caprylyl Glycol, Chlorphenesin, Phenoxyethanol.

Other information

- Protect this product from excessive heat and direct sun

Questions or comments

Call toll free 1-800-831-5150 in the US

PRINCIPAL DISPLAY PANEL - 30 mL Bottle Carton

special
clearing
booster

dermalogica®

acne treatment

mediBac clearing®

1 US Fl. Oz.
30 mL e